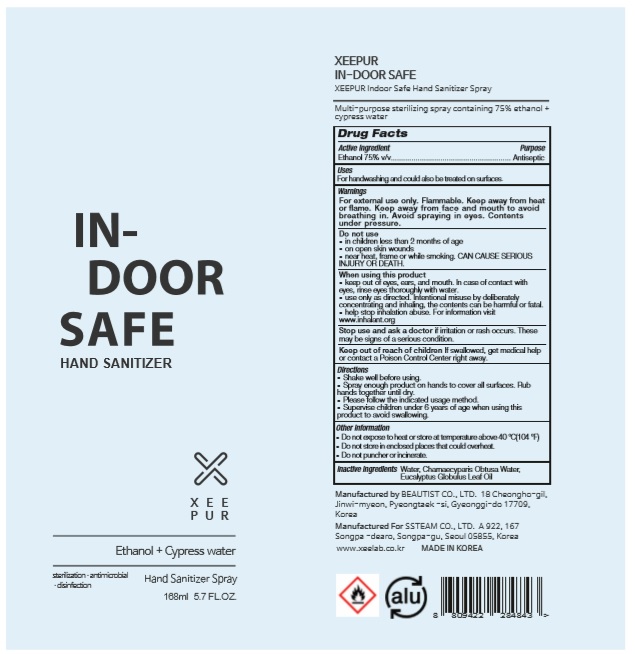 DRUG LABEL: XEEPUR INDOOR SAFE HAND SANITIZER
NDC: 70987-750 | Form: SPRAY
Manufacturer: BEAUTIST CO., LTD.
Category: otc | Type: HUMAN OTC DRUG LABEL
Date: 20200504

ACTIVE INGREDIENTS: ALCOHOL 126 mL/168 mL
INACTIVE INGREDIENTS: CHAMAECYPARIS OBTUSA WOOD OIL; EUCALYPTUS OIL; WATER

[XEEPUR INDOOR SAFE HAND SANITIZER] 168 ml : 70987-750-01